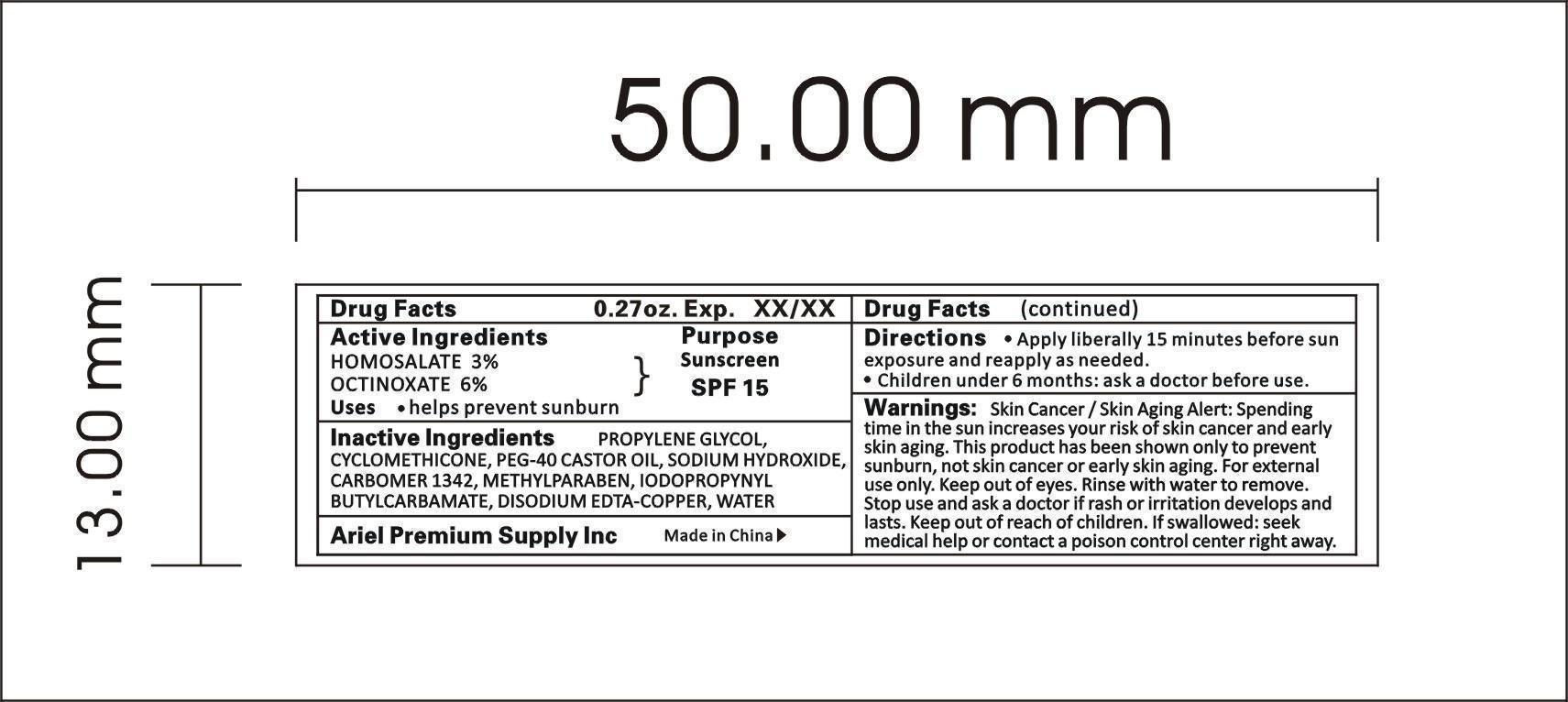 DRUG LABEL: SUN BLOCK SPRARY
NDC: 47993-215 | Form: SPRAY
Manufacturer: NINGBO JIANGBEI OCEAN STAR TRADING CO.,LTD
Category: otc | Type: HUMAN OTC DRUG LABEL
Date: 20191022

ACTIVE INGREDIENTS: HOMOSALATE 3 g/100 g; OCTINOXATE 6 g/100 g
INACTIVE INGREDIENTS: CYCLOMETHICONE 6 g/100 g; PEG-40 CASTOR OIL 1 g/100 g; DISODIUM EDTA-COPPER 0.03 g/100 g; CARBOMER 1342 0.2 g/100 g; PROPYLENE GLYCOL 8 g/100 g; SODIUM HYDROXIDE 0.5 g/100 g; IODOPROPYNYL BUTYLCARBAMATE 0.07 g/100 g; METHYLPARABEN 0.15 g/100 g; WATER 75.05 g/100 g

Active Ingredients

Active ingredients--------------purpose

HOMOSALATE 3%------------Sunscreen SPF15

OCTINOXATE 6%

Uses:
help prevent sunburn

Warnings:

Skin Cancer / Skin Aging Alert: Spending time in the sun increases your risk of skin cancer and early skin aging. This product has been shown only to prevent sunburn, not skin cancer or early skin aging. For external use only. Kepp out of eyes. Rinse with water to remove. Stop use and ask a doctor if rash or irritation develops and lasts. Keep out of reach of children. If swallowed: seek medical help or contact a poison control center right away.

Directions:

Apply liberally 15mintues before sun exposure and reapply as needed.

KEEP OUT OF REACH OF CHILDREN

Children under 6 months: ask a doctor before use.

Inactive Ingredients:

PROPYLENE GLYCOL, CYCLOMETHICONE, PEG-40 CASTOR OIL, SODIUM HYDROXIDE, CARBOMER 1342, METHYLPARABEN, IODOPROPYNYL BUTYLCARBAMATE, DISODIUM EDTA-COPPER, WATER